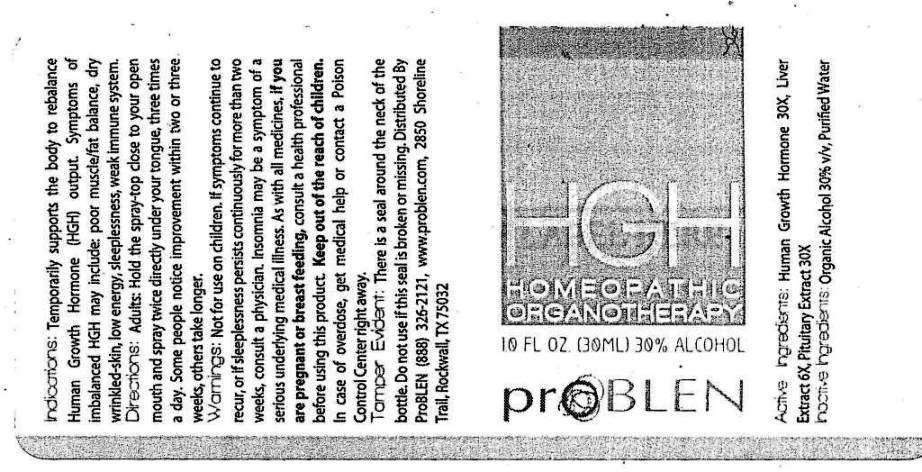 DRUG LABEL: HGH
NDC: 43853-0013 | Form: SPRAY
Manufacturer: ProBLEN
Category: homeopathic | Type: HUMAN OTC DRUG LABEL
Date: 20161123

ACTIVE INGREDIENTS: SOMATROPIN 30 [hp_X]/1 mL; SUS SCROFA PITUITARY GLAND 30 [hp_X]/1 mL; PORK LIVER 6 [hp_X]/1 mL
INACTIVE INGREDIENTS: WATER; ALCOHOL

Drug Facts:

ACTIVE INGREDIENTS:

Human Growth Hormone (2 Parts) 30X, Hypophysis Suis (2 Parts) 30X, Hepar Suis (1 Part) 6X

INDICATIONS:

Temporarily supports the body to rebalance Human Growth Hormone (HGH) output. Symptoms of imbalanced HGH may include: poor muscle/fat balance, dry wrinkled-skin, low energy, sleeplessness, weak immune system.

WARNINGS:

Not for use on children.

If symptoms continue to recur, or if sleeplessness persists continuously for more than two weeks, consult a physician. Insomnia may be a symptom of a serious underlying medical illness.

As with all medicines, if you are pregnant or breast feeding, consult a health professional before using this product.

Keep out of the reach of children. In case of overdose, get medical help or contact a Poison Control Center right away.

Tamper Evident. There is a seal around the neck of the bottle. Do not use if this seal is broken or missing.

KEEP OUT OF REACH OF CHILDREN:

Keep out of the reach of children. In case of overdose, get medical help or contact a Poison Control Center right away.

DIRECTIONS:

Adults: Hold the spray-top close to your open mouth and spray twice directly under your tongue, three times a day. Some people notice improvement within two or three weeks, others take longer.

INDICATIONS:

Temporarily supports the body to rebalance Human Growth Hormone (HGH) output. Symptoms of imbalanced HGH may include: poor muscle/fat balance, dry wrinkled-skin, low energy, sleeplessness, weak immune system.

INACTIVE INGREDIENTS:

Organic Alcohol 20% v/v, Purified Water

QUESTIONS:

Distributed By ProBLEN (888) 326-2121 www.problen.com
2850 Shoreline Trail, Suite 300, Rockwall, TX 75032

PACKAGE LABEL DISPLAY:

HGH

HOMEOPATHIC ORGANOTHERAPY

1.0 FL. OZ. (30 ML)

proBLEN